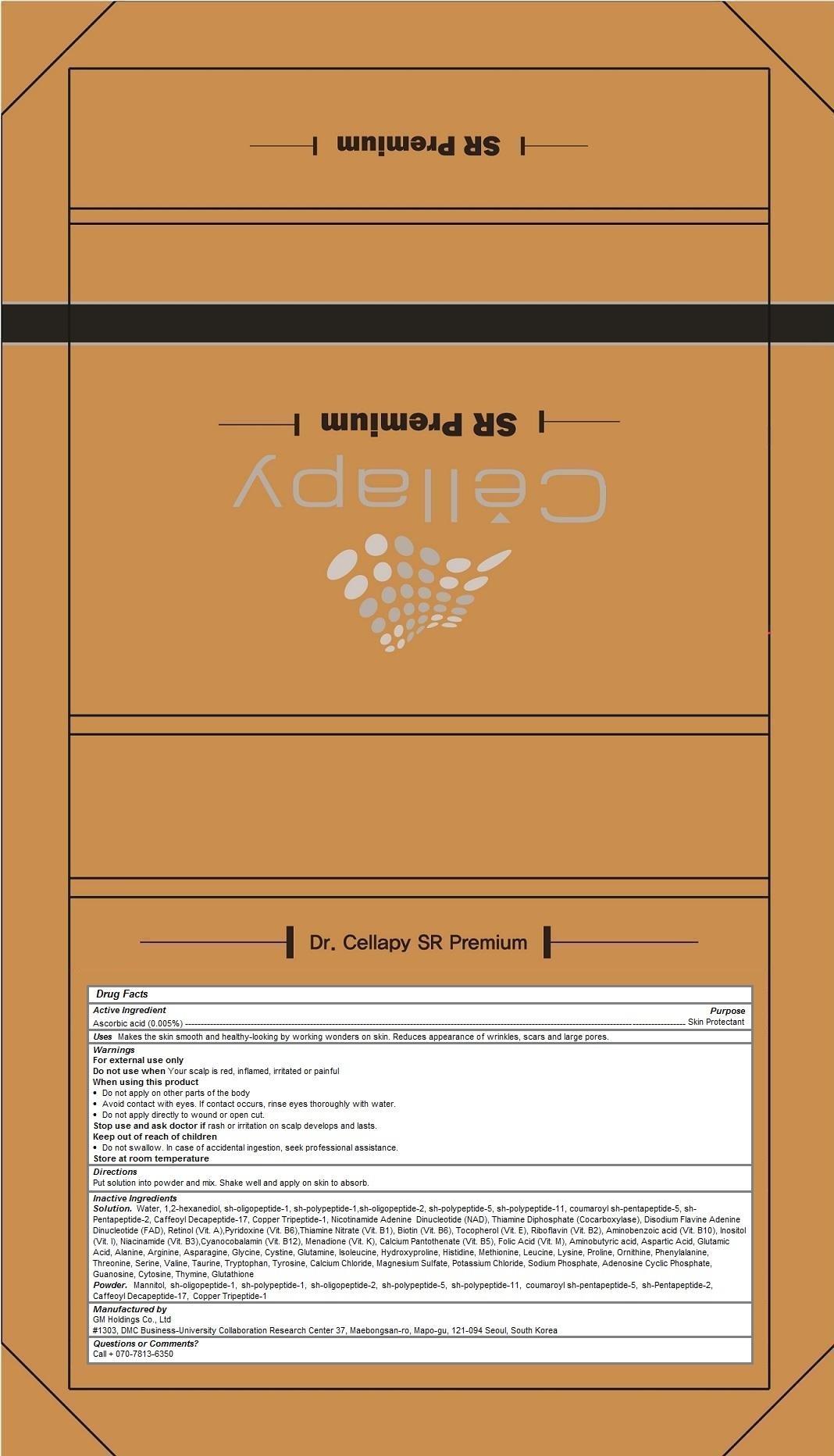 DRUG LABEL: Dr Cellapy SR Premium
NDC: 69278-100 | Form: KIT | Route: TOPICAL
Manufacturer: GM Holdings Co., Ltd
Category: otc | Type: HUMAN OTC DRUG LABEL
Date: 20200121

ACTIVE INGREDIENTS: ASCORBIC ACID 0.005 1/5 mL
INACTIVE INGREDIENTS: WATER; 1,2-HEXANEDIOL; NEPIDERMIN; BASIC FIBROBLAST GROWTH FACTOR (HUMAN); MECASERMIN; FIBROBLAST GROWTH FACTOR-1; PREZATIDE COPPER; NADIDE; COCARBOXYLASE; FLAVIN ADENINE DINUCLEOTIDE; RETINOL; PYRIDOXINE; THIAMINE MONONITRATE; BIOTIN; TOCOPHEROL; RIBOFLAVIN; AMINOBENZOIC ACID; INOSITOL; NIACINAMIDE; CYANOCOBALAMIN; MENADIONE; CALCIUM PANTOTHENATE; FOLIC ACID; .GAMMA.-AMINOBUTYRIC ACID; ASPARTIC ACID; GLUTAMIC ACID; ALANINE; ARGININE; ASPARAGINE; GLYCINE; CYSTINE; GLUTAMINE; ISOLEUCINE; HYDROXYPROLINE; HISTIDINE; METHIONINE; LEUCINE; LYSINE; PROLINE; ORNITHINE; PHENYLALANINE; THREONINE; SERINE; VALINE; TAURINE; TRYPTOPHAN; TYROSINE; CALCIUM CHLORIDE; MAGNESIUM SULFATE, UNSPECIFIED FORM; POTASSIUM CHLORIDE; SODIUM PHOSPHATE; ADENOSINE CYCLIC PHOSPHATE; GUANOSINE; CYTOSINE; THYMINE; GLUTATHIONE

Dr. Cellapy SR Premium